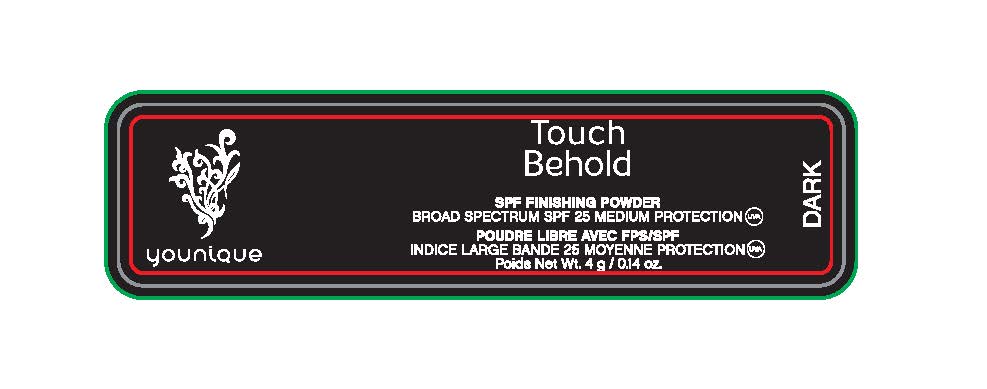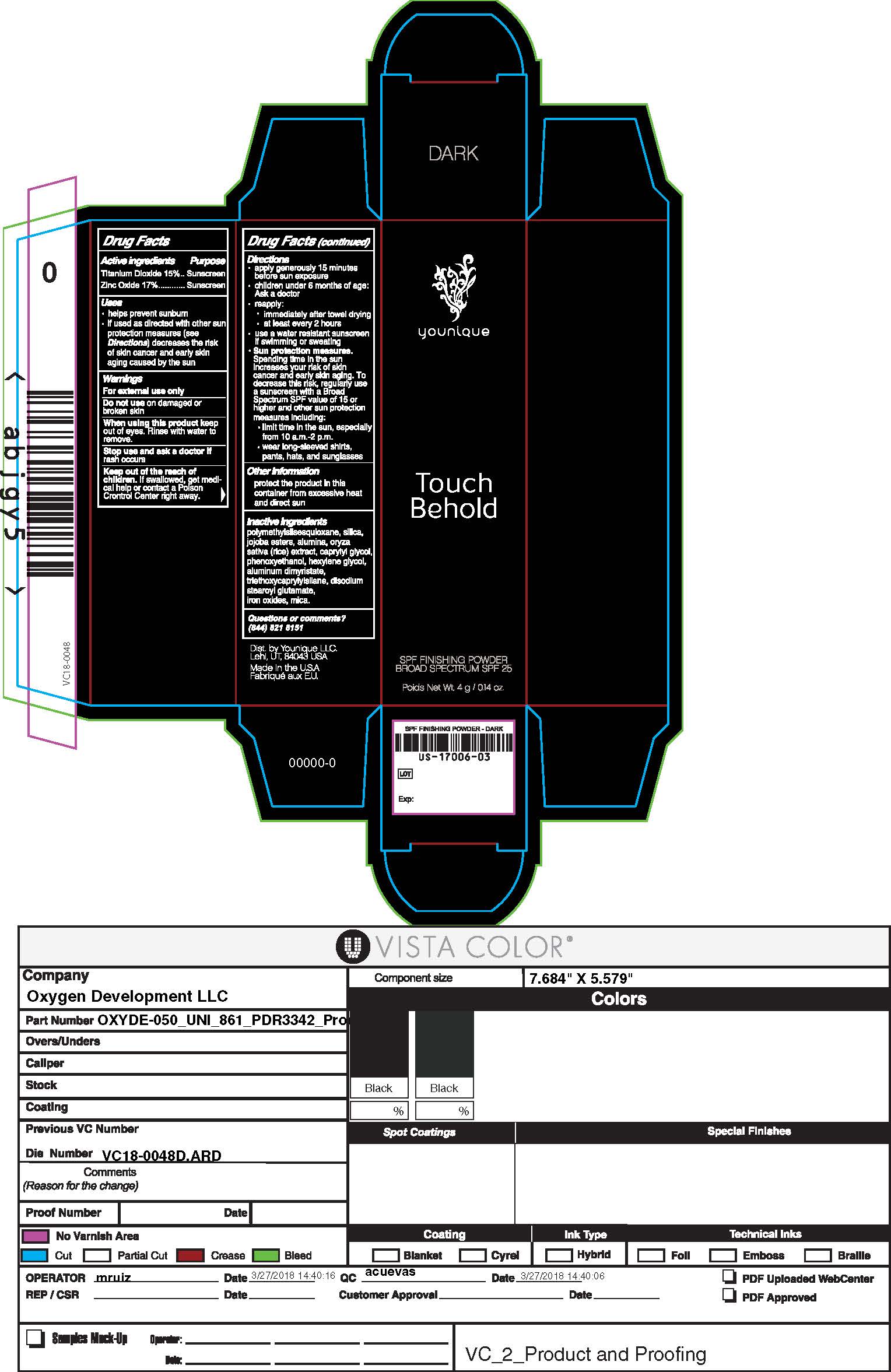 DRUG LABEL: powder
NDC: 61354-061 | Form: POWDER
Manufacturer: Oxygen Development
Category: otc | Type: HUMAN OTC DRUG LABEL
Date: 20230210

ACTIVE INGREDIENTS: TITANIUM DIOXIDE 15.09 g/100 g; ZINC OXIDE 17.55 g/100 g
INACTIVE INGREDIENTS: JOJOBA OIL; MICA; SILICON DIOXIDE; POLYMETHYLSILSESQUIOXANE (4.5 MICRONS)

Touch Behold SPF FINISHING POWDER BROAD SPECTRUM SPF 25

Active ingredient

Titanium Dioxide 15%

Zinc oxide 17%

Purpose

Sunscreen

Uses

Help precent sunburn. If used as directed with other sun protection measures (see directions) decreases the risk of skin cancer and early skin again caused by the sun

Warnings

For external use only

Do not use on damaged or broken skin

When using

When using this product keep out of eyes. Rinse with water to remove.

Stop use

Stop use and ask a doctor if rash occurs

Keep out of the reach of children

If swallowed, get medical help or contact a poison controler center right away

Directions

Apply generously 15 minutes before sun exposure. Children under 6 months of age: ask a doctor.

Reapply: immediately after towel drying. At least every 2 hours. Use a water resistant sunscreen if swimming or sweating. Sun protections measures. Spending time in the sun increases your risk of skin cancer and early skin aging. To decrease this risk, regularly use a sunscreen with a broad Spectrum SPF value of 15 or higher and other sun protection measures including: lomit time in the sun, especially from 10 a.m-2p.m. wear long-sleeved shirts, pants, hats, and sunglasses

Other information

protect the product in this container from excessive heat and direct sun

Iniactive ingredient

pollymethylsilsesquoxane, silica, jojoba esters, alumina, oryza sativa (rice)extract, caprylyl glycol, phenoxyethanol, hexylene glycol, aluminum dimyristate, triethoxycaprylylsilane, disodium stearoyl glutamate, iron oxides, mica.

Questions or Comments

(844) 821 8151